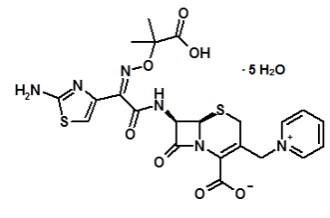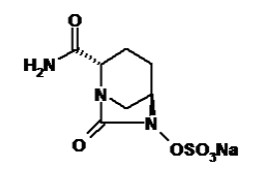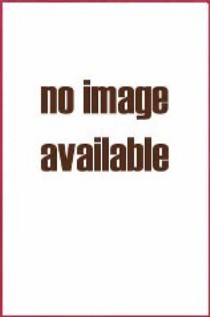 DRUG LABEL: AVYCAZ
NDC: 0456-2700 | Form: POWDER, FOR SOLUTION
Manufacturer: Allergan, Inc.
Category: prescription | Type: HUMAN PRESCRIPTION DRUG LABEL
Date: 20250425

ACTIVE INGREDIENTS: CEFTAZIDIME 2 g/1 1; AVIBACTAM SODIUM 0.5 g/1 1
INACTIVE INGREDIENTS: SODIUM CARBONATE 146 mg/1 1

HIGHLIGHTS OF PRESCRIBING INFORMATION

These highlights do not include all the information needed to use AVYCAZ® safely and effectively. See full prescribing information for AVYCAZ.
AVYCAZ (ceftazidime and avibactam) for injection, for intravenous use
Initial U.S. Approval: 2015

1 INDICATIONS AND USAGE

AVYCAZ is a combination of ceftazidime, a cephalosporin, and avibactam, a beta-lactamase inhibitor, indicated for the treatment of the following infections caused by designated susceptible Gram-negative microorganisms in adult and pediatric patients (at least 31 weeks gestational age):

- Complicated Intra-abdominal Infections (cIAI), used in combination with metronidazole (1.1)
- Complicated Urinary Tract Infections (cUTI), including Pyelonephritis (1.2)
- Hospital-acquired Bacterial Pneumonia and Ventilator-associated Bacterial Pneumonia (HABP/VABP) (1.3)

To reduce the development of drug-resistant bacteria and maintain the effectiveness of AVYCAZ and other antibacterial drugs, AVYCAZ should be used only to treat or prevent infections that are proven or strongly suspected to be caused by susceptible bacteria. (1.4)

2 DOSAGE AND ADMINISTRATION

Dosage of AVYCAZ in Adult Patients with Creatinine Clearance (CrCl) greater than 50 mL/min (2.1)

Infection

Dose

Frequency

Infusion Time

cIAI*, cUTI including Pyelonephritis, and HABP/VABP

AVYCAZ 2.5 grams (ceftazidime 2 grams and avibactam
0.5 grams)

Every 8 hours

2 hours

*Used in conjunction with metronidazole 0.5 g intravenously every 8 hours in adult cIAI patients

Dosage of AVYCAZ in Pediatric Patients aged 2 years to less than 18 years with Estimated Glomerular Filtration Rate (eGFR) greater than 50 mL/min/1.73 m^2 and in Pediatric Patients less than 2 years of age without Renal Impairment (2.2)
Infection | Age Range | Dose | Infusion Time/ Frequency
cIAI*, cUTI including Pyelonephritis, HABP/VABP | 2 years to less than 18 years | AVYCAZ 62.5 mg/kg to a maximum of 2.5 grams (ceftazidime 50 mg/kg and avibactam 12.5 mg/kg to a maximum dose of ceftazidime 2 grams and avibactam 0.5 grams) | 2 hours/ Every 8 hours
 | 6 months to less than 2 years | AVYCAZ 62.5 mg/kg (ceftazidime 50 mg/kg and avibactam 12.5 mg/kg)
 | 3 months to less than 6 months | AVYCAZ 50 mg/kg (ceftazidime 40 mg/kg and avibactam 10 mg/kg)
 | Greater than 28 daysa to less than 3 months | AVYCAZ 37.5 mg/kg (ceftazidime 30 mg/kg and avibactam 7.5 mg/kg)
 | Less than or equal to 28 daysb with GA 31 weeks and older | AVYCAZ 25 mg/kg (ceftazidime 20 mg/kg and avibactam 5 mg/kg)

*Used in conjunction with metronidazole 10 mg/kg intravenously every 8 hours in pediatric cIAI patients

aIncludes full-term infants with PNA > 28 days and pre-term infants with corrected age > 28 days. Corrected age is calculated by subtracting the number of weeks born before 40 weeks of gestation from the postnatal age.

bIncludes neonates PNA ≤ 28 days and pre-term infants with corrected age ≤ 28 days.

GA = gestational age and PNA = postnatal age.

- For treatment of cIAI, metronidazole should be given concurrently
- Recommended duration of treatment in adult and pediatric patients: (2.1, 2.2)
  - cIAI: 5 to 14 days
  - cUTI including pyelonephritis: 7 to 14 days
  - HABP/VABP: 7 to 14 days

- Dosage adjustment is required in adult patients with creatinine clearance (CrCl) less than or equal to 50 mL/min and in pediatric patients aged 2 years and older with renal impairment. There is insufficient information to recommend a dosing regimen for pediatric patients younger than 2 years of age with renal impairment. See Full Prescribing Information for additional information. (2.3)
- See Full Prescribing Information for instructions for constituting supplied dry powder and subsequent required dilution. (2.4)
- See Full Prescribing Information for drug compatibilities. (2.5)

3 DOSAGE FORMS AND STRENGTHS

AVYCAZ 2.5g (ceftazidime and avibactam) for injection is supplied as a sterile powder for constitution in single-dose vials containing ceftazidime 2 grams and avibactam 0.5 grams. (3)

4 CONTRAINDICATIONS

AVYCAZ is contraindicated in patients with known serious hypersensitivity to the components of AVYCAZ (ceftazidime and avibactam), avibactam-containing products or other members of the cephalosporin class. (4)

5 WARNINGS AND PRECAUTIONS

- Decreased Clinical Response in Adult cIAI Patients with Baseline CrCl of 30 to Less Than or Equal to 50 mL/ min: Monitor CrCl at least daily in adult and pediatric patients with changing renal function and adjust the dosage of AVYCAZ accordingly. (5.1)
- Hypersensitivity Reactions: Includes anaphylaxis and serious skin reactions. Cross sensitivity may occur in patients with a history of penicillin allergy. If an allergic reaction occurs, discontinue AVYCAZ. (5.2)
- Clostridioides difficile-associated Diarrhea (CDAD): CDAD has been reported with nearly all systemic antibacterial agents, including AVYCAZ. Evaluate if diarrhea occurs. (5.3)
- Central Nervous System Reactions: Seizures and other neurologic events may occur, especially in patients with renal impairment. Adjust dose in patients with renal impairment. (5.4)

6 ADVERSE REACTIONS

- Adult Patients: The most common adverse reactions in cIAI (≥ 5%, when used with metronidazole) patients are diarrhea, nausea and vomiting. The most common adverse reactions (3%) in cUTI patients are diarrhea and nausea. The most common adverse reactions (≥ 5%) in HABP/VABP patients were diarrhea and vomiting. (6.1)
- Pediatric Patients (aged 3 months to less than 18 years): The most common adverse reactions (≥ 3%) in pediatric patients aged 3 months and older were vomiting, diarrhea, rash, and infusion site phlebitis. (6.1)
- Pediatric Patients (less than 3 months of age): The most common adverse reactions (>3 %) in pediatric patients less than 3 months of age were vomiting and increased transaminases. (6.1)

To report SUSPECTED ADVERSE REACTIONS, contact AbbVie at 1-800-633-9110 or FDA at 1-800-FDA-1088 or www.fda.gov/medwatch.

FULL PRESCRIBING INFORMATION

1 INDICATIONS AND USAGE

1.1 Complicated Intra-abdominal Infections (cIAI)

AVYCAZ (ceftazidime and avibactam) in combination with metronidazole, is indicated for the treatment of complicated intra-abdominal infections (cIAI) in adult and pediatric patients (at least 31 weeks gestational age) caused by the following susceptible gram-negative microorganisms: Escherichia coli, Klebsiella pneumoniae, Proteus mirabilis, Enterobacter cloacae, Klebsiella oxytoca, Citrobacter freundii complex, and Pseudomonas aeruginosa.

1.2 Complicated Urinary Tract Infections (cUTI), including Pyelonephritis

AVYCAZ (ceftazidime and avibactam) is indicated for the treatment of complicated urinary tract infections (cUTI) including pyelonephritis in adult and pediatric patients (at least 31 weeks gestational age) caused by the following susceptible gram-negative microorganisms: Escherichia coli, Klebsiella pneumoniae, Enterobacter cloacae, Citrobacter freundii complex, Proteus mirabilis, and Pseudomonas aeruginosa.

1.3 Hospital-acquired Bacterial Pneumonia and Ventilator-associated Bacterial Pneumonia (HABP/VABP)

AVYCAZ (ceftazidime and avibactam) is indicated for the treatment of hospital-acquired bacterial pneumonia and ventilator-associated bacterial pneumonia (HABP/VABP) in adult and pediatric patients (at least 31 weeks gestational age) caused by the following susceptible gram-negative microorganisms: Klebsiella pneumoniae, Enterobacter cloacae, Escherichia coli, Serratia marcescens, Proteus mirabilis, Pseudomonas aeruginosa, and Haemophilus influenzae.

1.4 Usage

To reduce the development of drug-resistant bacteria and maintain the effectiveness of AVYCAZ and other antibacterial drugs, AVYCAZ should be used only to treat or prevent infections that are proven or strongly suspected to be caused by susceptible bacteria. When culture and susceptibility information are available, they should be considered in selecting or modifying antibacterial therapy. In the absence of such data, local epidemiology and susceptibility patterns may contribute to the empiric selection of therapy.

2 DOSAGE AND ADMINISTRATION

2.1 Recommended Dosage in Adult Patients

The recommended dosage of AVYCAZ is 2.5 grams (ceftazidime 2 grams and avibactam 0.5 grams) administered every 8 hours by intravenous (IV) infusion over 2 hours in patients 18 years of age and older with CrCl greater than 50 mL/min. For treatment of cIAI, metronidazole should be given concurrently. The guidelines for dosage of AVYCAZ in patients with creatinine clearance (CrCl) greater than 50 mL/min are listed in Table 1.

Table 1. Dosage of AVYCAZ 2.5 grams (ceftazidime 2 grams and avibactam 0.5 grams) by Indication in Adult Patients (18 years of age and older)
Infection | Dose | Frequency | Infusion Time (hours) | Duration of Treatment
Complicated Intra-abdominal Infections (cIAI)* | 2.5 grams | Every 8 hours | 2 | cIAI: 5 to 14 days cUTI: 7 to 14 days HABP/VABP: 7 to 14 days
Complicated Urinary Tract Infections including Pyelonephritis (cUTI)
Hospital-acquired Bacterial Pneumonia and Ventilator-associated Bacterial Pneumonia (HABP/VABP)
* Used in conjunction with metronidazole 0.5 g intravenously every 8 hours in adult cIAI patients [see Clinical Studies (14.1)].

2.2 Recommended Dosage in Pediatric Patients

The recommended dosage of AVYCAZ in pediatric patients aged 2 years to less than 18 years and an estimated glomerular filtration rate (eGFR) greater than 50 mL/min/1.73 m^2 and in pediatric patients less than 2 years of age without renal impairment is described in Table 2. AVYCAZ is administered every 8 hours by intravenous infusion over 2 hours. For treatment of cIAI, metronidazole should be given concurrently.

Table 2. Dosage of AVYCAZ (ceftazidime and avibactam) in Pediatric Patients
Infection | Age Range | Dose | Frequency | Infusion Time (hours) | Duration of treatment
cIAI*, cUTI including Pyelonephritis, and HABP/VABP | 2 years to less than 18 yearsa | AVYCAZ 62.5 mg/kg to a maximum of 2.5 grams (ceftazidime 50 mg/kg and avibactam 12.5 mg/kg to a maximum dose of ceftazidime 2 grams and avibactam 0.5 grams) | Every 8 hours | 2 | cIAI: 5 to 14 days cUTI: 7 to 14 days HABP/VABP: 7 to 14 days
 | 6 months to less than 2 years | AVYCAZ 62.5 mg/kg (ceftazidime 50 mg/kg and avibactam 12.5 mg/kg)
 | 3 months to less than 6 months | AVYCAZ 50 mg/kg (ceftazidime 40 mg/kg and avibactam 10 mg/kg)
 | Greater than 28 daysb to less than 3 months | AVYCAZ 37.5 mg/kg (ceftazidime 30 mg/kg and avibactam 7.5 mg/kg)
 | Less than or equal to 28 daysc with GA 31 weeks and older | AVYCAZ 25 mg/kg (ceftazidime 20 mg/kg and avibactam 5 mg/kg)
*AVYCAZ was used in conjunction with metronidazole 10 mg/kg intravenously every 8 hours in pediatric cIAI patients [see Clinical Studies (14.1)]
a For pediatric patients (aged 2 years and older) with eGFR less than or equal to 50 mL/min/1.73m^2, dosage adjustments are recommended [see Dosage and Administration (2.3)].
b Includes full-term infants with PNA > 28 days and pre-term infants with corrected age > 28 days. Corrected age is calculated by subtracting the number of weeks born before 40 weeks of gestation from the postnatal age.
c Includes neonates PNA ≤ 28 days and pre-term infants with corrected age ≤ 28 days.
GA = gestational age and PNA = postnatal age.

2.3 Dosage Adjustments in Adult and Pediatric Patients (Aged 2 Years and Older) with Renal Impairment

The recommended AVYCAZ dosage in adult and pediatric patients aged 2 years and older with varying degrees of renal function is presented in Table 3 and Table 4, respectively. For patients with changing renal function, monitor CrCl in adults or eGFR in pediatric patients at least daily and adjust the dosage of AVYCAZ accordingly [see Warnings and Precautions (5.1), Use in Specific Populations (8.6) and Clinical Pharmacology (12.3)]. There is insufficient information to recommend a dosing regimen for pediatric patients less than 2 years of age with renal impairment.

Adult Patients

Table 3. Dosage of AVYCAZ in Adult Patients with Renal Impairment
Estimated Creatinine Clearance (mL/minute) a | Dose for AVYCAZ (ceftazidime and avibactam) b | Frequency
31 to 50 | AVYCAZ 1.25 grams (ceftazidime 1 gram and avibactam 0.25 grams) intravenously | Every 8 hours
16 to 30 | AVYCAZ 0.94 grams (ceftazidime 0.75 grams and avibactam 0.19 grams) intravenously | Every 12 hours
6 to 15c | AVYCAZ 0.94 grams (ceftazidime 0.75 grams and avibactam 0.19 grams) intravenously | Every 24 hours
Less than or equal to 5c | AVYCAZ 0.94 grams (ceftazidime 0.75 grams and avibactam 0.19 grams) intravenously | Every 48 hours
a As calculated using the Cockcroft-Gault formula
b All doses of AVYCAZ are administered over 2 hours
c Both ceftazidime and avibactam are hemodialyzable; thus, administer AVYCAZ after hemodialysis on hemodialysis days

Pediatric Patients

Table 4. Dosage of AVYCAZ in Pediatric Patients Aged 2 years and older with Renal Impairmenta
Estimated eGFRb (mL/min/1.73m^2) | Dose for AVYCAZ (ceftazidime and avibactam) c | Frequency
31 to 50 | AVYCAZ 31.25 mg/kg to a maximum of 1.25 grams (ceftazidime 25 mg/kg and avibactam 6.25 mg/kg to a maximum dose of ceftazidime 1 gram and avibactam 0.25 grams) | Every 8 hours
16 to 30 | AVYCAZ 23.75 mg/kg to a maximum of 0.94 grams (ceftazidime 19 mg/kg and avibactam 4.75 mg/kg to a maximum dose of ceftazidime 0.75 grams and avibactam 0.19 grams) | Every 12 hours
6 to 15 | AVYCAZ 23.75 mg/kg to a maximum of 0.94 grams (ceftazidime 19 mg/kg and avibactam 4.75 mg/kg to a maximum dose of ceftazidime 0.75 grams and avibactam 0.19 grams) | Every 24 hours
Less than or equal to 5d | AVYCAZ 23.75 mg/kg to a maximum of 0.94 grams (ceftazidime 19 mg/kg and avibactam 4.75 mg/kg to a maximum dose of ceftazidime 0.75 grams and avibactam 0.19 grams) | Every 48 hours
a Dosing was derived based on the population PK modeling, which assumed similar proportional effects of renal impairment in adults and pediatric
patients aged 2 years and older [see Clinical Pharmacology (12.3)]
b As calculated using the Schwartz bedside formula
c All doses of AVYCAZ are administered over 2 hours
d Both ceftazidime and avibactam are hemodialyzable; thus, administer AVYCAZ after hemodialysis on hemodialysis days

2.4 Preparation of the AVYCAZ Solution for Administration

AVYCAZ is supplied as a dry powder, which must be constituted and subsequently diluted, using aseptic technique prior to intravenous infusion.

a) Constitute the powder in the AVYCAZ vial with 10 mL of one of the following solutions:

- sterile water for injection, USP
- 0.9% of sodium chloride injection, USP (normal saline)
- 5% of dextrose injection, USP
- all combinations of dextrose injection and sodium chloride injection, USP, containing up to 2.5% dextrose, USP, and 0.45% sodium chloride, USP, or
- lactated Ringer’s injection, USP

b) Mix gently and ensure that the contents are dissolved completely. The constituted AVYCAZ solution will have an approximate ceftazidime concentration of 167 mg/mL and an approximate avibactam concentration of 42 mg/mL. The final volume is approximately 12 mL. The constituted solution is not for direct injection. The constituted solution must be diluted before intravenous infusion.

c) Prepare the required dose for intravenous infusion by withdrawing the appropriate volume determined from Table 5 from the constituted vial. To prepare doses for pediatric patients weighing less than 40 kg, follow the constitution instruction above to yield a solution with a final AVYCAZ concentration of approximately 209 mg/mL (ceftazidime concentration of 167 mg/mL and an avibactam concentration of 42 mg/mL). Use these concentrations to calculate the volume of AVYCAZ required to prepare the prescribed dose.

Table 5. Preparation of AVYCAZ Doses for Adult and Pediatric Patients (Weighing 40 kg or More)
AVYCAZ (ceftazidime and avibactam) Dose | Volume to Withdraw from Constituted Vial for Further Dilution to 50 to 250 a mL
2.5 grams (2 grams and 0.5 grams) | 12 mL (entire contents)
1.25 grams (1 gram and 0.25 grams) | 6 mL
0.94 grams (0.75 grams and 0.19 grams) | 4.5 mL
a. Dilution to 250 mL should only be used for the 2.5 gram dose

d) Before infusion, dilute the withdrawn volume of the constituted AVYCAZ solution further with the same diluent used for constitution of the powder (except sterile water for injection), to achieve a ceftazidime concentration of 8 to 40 mg/mL and an avibactam concentration of 2 to 10 mg/mL in an infusion bag. If sterile water for injection was used for constitution, use any of the other appropriate constitution diluents for dilution.

e) Mix gently and ensure that the contents are dissolved completely. Visually inspect the diluted AVYCAZ solution (for administration) for particulate matter and discoloration prior to administration (the color of the AVYCAZ infusion solution for administration ranges from clear to light yellow).

f) Use the diluted AVYCAZ solution in the infusion bags within 12 hours when stored at room temperature.

g) The diluted AVYCAZ solution in the infusion bags may be stored under refrigeration at 2 to 8°C (36 to 46°F) up to 24 hours following dilution and used within 12 hours of subsequent storage at room temperature.

2.5 Drug Compatibility

The AVYCAZ solution for administration at the range of diluted concentrations of ceftazidime 8 mg/mL and avibactam 2 mg/mL to ceftazidime 40 mg/mL and avibactam 10 mg/mL is compatible with the more commonly used intravenous infusion fluids in infusion bags (including Baxter® Mini-Bag Plus™) such as:

- 0.9% sodium chloride injection, USP
- 5% dextrose injection, USP
- all combinations of dextrose injection and sodium chloride injection, USP, containing up to 2.5% dextrose, USP, and 0.45% sodium chloride, USP
- lactated ringer's injection, USP, and
- Baxter® Mini-Bag Plus™ containing 0.9% sodium chloride injection or 5% dextrose injection

Intravenous Line Compatibility

Simulated Y-site compatibility of AVYCAZ admixed with other drug products in a 1:1 volume ratio at room temperature was evaluated by visual inspection, and measurement of turbidity and particulate matter at 0, 1 and 4 hours after mixing. Ceftazidime and avibactam were tested at concentrations of 20 mg/mL and 5 mg/mL, respectively, which can be obtained by dilution of constituted AVYCAZ solution in a 100 mL intravenous infusion bag. The highest recommended concentration (40 mg/mL of ceftazidime and 10 mg/mL of avibactam) was not tested in this study and should not be used during co-administration of AVYCAZ with other drugs through the same intravenous line. Compatible drugs with the corresponding compatible diluent (i.e., 0.9% Sodium Chloride Injection, 5 % Dextrose Injection or Lactated Ringer’s Injection) are listed in Tables 6, 7, 8 and 9 below. Any drug products not listed in the tables below should not be co-administered with AVYCAZ through the same intravenous line (or cannula).

Table 6. Compatible Drugs for use with 0.9% Sodium Chloride, 5% Dextrose or Lactated Ringer’s Injection as Diluents

Daptomycin

Dexmedetomidine Injection

Dopamine Hydrochloride Injection

Furosemide Injection

Gentamicin Injection

Imipenem and Cilastatin for Injection

Magnesium Sulfate Injection

Norepinephrine Bitartrate Injection

Phenylephrine Hydrochloride Injection

Vasopressin Injection

Vecuronium Bromide

Metronidazole Injection

Aztreonam Injection or Aztreonam for Injection

Colistimethate for Injection

Amikacin Sulfate Injection

Azithromycin for Injection

Ceftaroline fosamil for Injection

Levofloxacin

Table 7. Compatible Drugs for use with 0.9% Sodium Chloride or 5% Dextrose Injection as Diluents

Ertapenem Sodium

Potassium Phosphates Injection

Table 8. Compatible Drugs for use with 5% Dextrose or Lactated Ringer’s Injection as Diluents

Heparin Sodium Injection

Linezolid Injection

Tobramycin Injection or Tobramycin for Injection

Table 9. Compatible Drugs for use with One Compatible Diluent only

Meropenem for Injection (0.9% Sodium Chloride Injection diluent only)

Sodium Bicarbonate Injection (5% Dextrose Injection diluent only)

Tedizolid Phosphate for Injection (5% Dextrose Injection diluent only)

Potassium Chloride in Water for Injection (40 mEq/100 mL) (Lactated Ringer’s Injection diluent only)

2.6 Storage of Constituted Solutions

Upon constitution with appropriate diluent, the constituted AVYCAZ solution may be held for no longer than 30 minutes prior to transfer and dilution in a suitable infusion bag.

Following dilution of the constituted solutions with the appropriate diluents, AVYCAZ solutions in the infusion bags are stable for 12 hours when stored at room temperature.

Following dilution of the constituted solutions with the appropriate diluents, AVYCAZ solutions in the infusion bags may also be refrigerated at 2 to 8°C (36 to 46°F) for up to 24 hours; and then should be used within 12 hours of subsequent storage at room temperature.

3 DOSAGE FORMS AND STRENGTHS

AVYCAZ 2.5 grams (ceftazidime and avibactam) for injection is supplied as a white to yellow sterile powder for constitution in a single-dose, sterile, clear glass vial containing ceftazidime 2 grams and avibactam 0.5 grams.

4 CONTRAINDICATIONS

AVYCAZ is contraindicated in patients with known serious hypersensitivity to the components of AVYCAZ (ceftazidime and avibactam), avibactam containing products, or other members of the cephalosporin class [see Warnings and Precautions (5.2)].

5 WARNINGS AND PRECAUTIONS

5.1 Decreased Clinical Response in Adult cIAI Patients with Baseline Creatinine Clearance of 30 to Less Than or Equal to 50 mL/min

In a Phase 3 cIAI trial in adult patients, clinical cure rates were lower in a subgroup of patients with baseline CrCl of 30 to less than or equal to 50 mL/min compared to those with CrCl greater than 50 mL/min (Table 10). The reduction in clinical cure rates was more marked in patients treated with AVYCAZ plus metronidazole compared to meropenem-treated patients. Within this subgroup, patients treated with AVYCAZ received a 33% lower daily dose than is currently recommended for patients with CrCl 30 to less than or equal to 50 mL/min.

The decreased clinical response was not observed for patients with moderate renal impairment at baseline (CrCl of 30 to less than or equal to 50 mL/min) in the Phase 3 cUTI trials or the Phase 3 HABP/VABP trial.

Monitor CrCl at least daily in adult and pediatric patients with changing renal function and adjust the dosage of AVYCAZ accordingly [see Dosage and Administration (2.2, 2.3), and Adverse Reactions (6.1)].

Table 10. Clinical Cure Rate at Test of Cure in a Phase 3 cIAI Trial, by Baseline Renal Function – mMITT Populationa
 | AVYCAZ + Metronidazole % (n/N) | Meropenem % (n/N)
Normal function / mild impairment (CrCl greater than 50 mL/min) | 85% (322/379) | 86% (321/373)
Moderate impairment (CrCl 30 to less than or equal to 50 mL/min) | 45% (14/31) | 74% (26/35)
a Microbiological modified intent-to-treat (mMITT) population included patients who had at least one bacterial pathogen at baseline and received at least one dose of study drug.

5.2 Hypersensitivity Reactions

Serious and occasionally fatal hypersensitivity (anaphylactic) reactions and serious skin reactions have been reported in patients receiving beta-lactam antibacterial drugs. Before therapy with AVYCAZ is instituted, careful inquiry about previous hypersensitivity reactions to other cephalosporins, penicillins, or carbapenems should be made. Exercise caution if this product is to be given to a penicillin or other beta-lactam-allergic patient because cross sensitivity among beta-lactam antibacterial drugs has been established. Discontinue the drug if an allergic reaction to AVYCAZ occurs.

5.3 Clostridioides difficile-associated Diarrhea

Clostridioides difficile-associated diarrhea (CDAD) has been reported for nearly all systemic antibacterial drugs, including AVYCAZ, and may range in severity from mild diarrhea to fatal colitis. Treatment with antibacterial drugs alters the normal flora of the colon and may permit overgrowth of C. difficile.

C. difficile produces toxins A and B which contribute to the development of CDAD. Hypertoxin producing strains of C. difficile cause increased morbidity and mortality, as these infections can be refractory to antimicrobial therapy and may require colectomy. CDAD must be considered in all patients who present with diarrhea following antibacterial use. Careful medical history is necessary because CDAD has been reported to occur more than 2 months after the administration of antibacterial drugs.

If CDAD is suspected or confirmed, antibacterial drugs not directed against C. difficile may need to be discontinued. Manage fluid and electrolyte levels as appropriate, supplement protein intake, monitor antibacterial treatment of C. difficile, and institute surgical evaluation as clinically indicated.

5.4 Central Nervous System Reactions

Seizures, nonconvulsive status epilepticus (NCSE), encephalopathy, coma, asterixis, neuromuscular excitability, and myoclonia have been reported in patients treated with ceftazidime, particularly in the setting of renal impairment. Adjust dosing based on creatinine clearance [see Dosage and Administration (2.2)].

5.5 Development of Drug-Resistant Bacteria

Prescribing AVYCAZ in the absence of a proven or strongly suspected bacterial infection or a prophylactic indication is unlikely to provide benefit to the patient and increases the risk of the development of drug-resistant bacteria [see Indications and Usage (1.4)].

6 ADVERSE REACTIONS

The following adverse reactions are discussed in greater detail in the Warnings and Precautions section:

- Hypersensitivity Reactions [see Warnings and Precautions (5.2)]
- Clostridioides difficile-Associated Diarrhea [see Warnings and Precautions (5.3)]
- Central Nervous System Reactions [see Warnings and Precautions (5.4)]

6.1 Clinical Trials Experience

Because clinical trials are conducted under widely varying conditions, adverse reaction rates observed in the clinical trials of a drug cannot be directly compared to rates in the clinical trials of another drug and may not reflect the rates observed in practice.

Clinical Trials Experience in Adult Patients

AVYCAZ was evaluated in six active-controlled clinical trials in patients with cIAI, cUTI, including pyelonephritis, or HABP/VABP. These trials included two Phase 2 trials, one in cIAI and one in cUTI, as well as four Phase 3 trials, one in cIAI, one in cUTI (Trial 1), one in cIAI or cUTI due to ceftazidime non-susceptible pathogens (Trial 2), and one in HABP/VABP. Data from cUTI Trial 1 served as the primary dataset for AVYCAZ safety findings in cUTI as there was a single comparator. cUTI Trial 2 had an open-label design as well as multiple comparator regimens which prevented pooling but provided supportive information. The six clinical trials included a total of 1809 adult patients treated with AVYCAZ and 1809 patients treated with comparators.

Complicated Intra-abdominal Infections

The Phase 3 cIAI trial included 529 adult patients treated with AVYCAZ 2.5 grams (ceftazidime 2 grams and avibactam 0.5 grams) administered intravenously over 120 minutes every 8 hours plus 0.5 grams metronidazole administered intravenously over 60 minutes every 8 hours and 529 patients treated with meropenem. The median age of patients treated with AVYCAZ was 50 years (range 18 to 90 years) and 22.5% of patients were 65 years of age or older. Patients were predominantly male (62%) and Caucasian (76.6%).

Treatment discontinuation due to an adverse reaction occurred in 2.6% (14/529) of patients receiving AVYCAZ plus metronidazole and 1.3% (7/529) of patients receiving meropenem.

Adverse reactions occurring at 5% or greater in patients receiving AVYCAZ plus metronidazole were diarrhea, nausea, and vomiting.

Table 11 lists adverse reactions occurring in 1% or more of patients receiving AVYCAZ plus metronidazole and with incidences greater than the comparator in the Phase 3 cIAI clinical trial.

Table 11. Incidence of Selected Adverse Reactions Occurring in 1% or more of Adult Patients (18 years of age and older) Receiving AVYCAZ in the Phase 3 cIAI Trial
Adverse Reactions | AVYCAZ plus metronidazolea (N=529) | Meropenemb (N=529)
Nervous system disorders
Headache | 3% | 2%
Dizziness | 2% | 1%
Gastrointestinal disorders
Diarrhea | 8% | 3%
Nausea | 7% | 5%
Vomiting | 5% | 2%
Abdominal Pain | 1% | 1%
a 2.5 grams (ceftazidime 2 grams and avibactam 0.5 grams) IV over 120 minutes every 8 hours (with metronidazole 0.5 grams IV every 8 hours)
b 1 gram IV over 30 minutes every 8 hours

Increased Mortality

In the Phase 3 cIAI trial, death occurred in 2.5% (13/529) of patients who received AVYCAZ plus metronidazole and in 1.5% (8/529) of patients who received meropenem. Among a subgroup of patients with baseline CrCl 30 to less than or equal to 50 mL/min, death occurred in 19.5% (8/41) of patients who received AVYCAZ plus metronidazole and in 7.0% (3/43) of patients who received meropenem. Within this subgroup, patients treated with AVYCAZ received a 33% lower daily dose than is currently recommended for patients with CrCl 30 to less than or equal to 50 mL/min [see Dosage and Administration (2.2) and Warnings and Precautions (5.1)]. In patients with normal renal function or mild renal impairment (baseline CrCl greater than 50 mL/min), death occurred in 1.0% (5/485) of patients who received AVYCAZ plus metronidazole and in 1.0% (5/484) of patients who received meropenem. The causes of death varied and contributing factors included progression of underlying infection, baseline pathogens isolated that were unlikely to respond to the study drug, and delayed surgical intervention.

Complicated Urinary Tract Infections, Including Pyelonephritis

The Phase 3 cUTI Trial 1 included 511 adult patients treated with AVYCAZ 2.5 grams (ceftazidime 2 grams and avibactam 0.5 grams) administered intravenously over 120 minutes every 8 hours and 509 patients treated with doripenem; in some patients parenteral therapy was followed by a switch to an oral antimicrobial agent [see Clinical Studies (14.2)]. Median age of patients treated with AVYCAZ was 54 years (range 18 to 89 years) and 30.7% of patients were 65 years of age or older. Patients were predominantly female (68.3%) and Caucasian (82.4%). Patients with CrCl less than 30 mL/min were excluded.

There were no deaths in Trial 1. Treatment discontinuation due to adverse reactions occurred in 1.4% (7/511) of patients receiving AVYCAZ and 1.2% (6/509) of patients receiving doripenem.

The most common adverse reactions occurring in 3% of cUTI patients treated with AVYCAZ were nausea and diarrhea.

Table 12 lists adverse reactions occurring in 1% or more of patients receiving AVYCAZ and with incidences greater than the comparator in Trial 1.

Table 12. Incidence of Selected Adverse Drug Reactions Occurring in 1% or more of Adult Patients (18 years of age and older) Receiving AVYCAZ in the Phase 3 cUTI Trial 1
Adverse Reactions | AVYCAZa (N=511) | Doripenemb (N=509)
Gastrointestinal disorders
Nausea | 3% | 2%
Diarrhea | 3% | 1%
Constipation | 2% | 1%
Upper abdominal pain | 1% | < 1%
a 2.5 grams (ceftazidime 2 grams and avibactam 0.5 grams) IV over 120 minutes every 8 hours
b 0.5 grams IV over 60 minutes every 8 hours

Hospital-acquired Bacterial Pneumonia/Ventilator-associated Bacterial Pneumonia

The Phase 3 HABP/VABP trial included 436 adult patients treated with AVYCAZ 2.5 grams (ceftazidime 2 grams and avibactam 0.5 grams) administered intravenously over 120 minutes and 434 patients treated with meropenem. The median age of patients treated with AVYCAZ was 66 years (range 18 to 89 years) and 54.1% of patients were 65 years of age or older. Patients were predominantly male (74.5%) and Asian (56.2%).

Death occurred in 9.6% (42/ 436) of patients who received AVYCAZ and in 8.3% (36/434) of patients who received meropenem. Treatment discontinuation due to an adverse reaction occurred in 3.7% (16/436) of patients receiving AVYCAZ and 3% (13/434) of patients receiving meropenem.

Adverse reactions occurring at 5% or greater in patients receiving AVYCAZ were diarrhea and vomiting.

Table 13 lists selected adverse reactions occurring in 1% or more of patients receiving AVYCAZ and with incidences greater than the comparator in the Phase 3 HABP/VABP clinical trial.

Table 13. Incidence of Selected Adverse Drug Reactions Occurring in 1% or more of Adult Patients (18 years of age and older) Receiving AVYCAZ in the Phase 3 HABP/VABP Trial
Adverse Reactions | AVYCAZa (N=436) | Meropenemb (N=434)
Gastrointestinal disorders
Nausea | 3% | 2%
Skin and subcutaneous tissue disorders
Pruritus | 2% | 1%
a 2.5 grams (ceftazidime 2 grams and avibactam 0.5 grams) IV over 120 minutes every 8 hours
b 1 gram IV over 30 minutes every 8 hours

Other Adverse Reactions of AVYCAZ and Ceftazidime in Adults

Direct Coombs’ Test Seroconversion with AVYCAZ

In the Phase 3 trials, seroconversion from a negative to a positive direct Coombs’ test result among patients with an initial negative Coombs’ test and at least one follow up test occurred in 3% (cUTI), 12.9% (cIAI), and 21.4% (HABP/VABP) of patients receiving AVYCAZ and 0.9% (cUTI), 3% (cIAI) and 7% (HABP/VABP) of patients receiving a carbapenem comparator.

Less Common Adverse Reactions with AVYCAZ

The following selected adverse reactions were reported in AVYCAZ-treated patients at a rate of less than 1% in the Phase 3 trials and are not described elsewhere in the labeling.

Blood and lymphatic disorders – Thrombocytopenia, Thrombocytosis, Leukopenia
General disorders and administration site conditions – Injection site phlebitis
Infections and infestations – Candidiasis
Investigations – Increased aspartate aminotransferase, Increased alanine aminotransferase, Increased gamma-glutamyl transferase
Metabolism and nutrition disorders – Hypokalemia
Nervous system disorders – Dysgeusia
Renal and urinary disorders – Acute kidney injury, Renal impairment, Nephrolithiasis
Skin and subcutaneous tissue disorders – Rash, Rash maculo-papular, Urticaria
Psychiatric disorders – Anxiety

Adverse Reactions with Ceftazidime

Additionally, adverse reactions reported with ceftazidime alone that were not reported in AVYCAZ-treated patients in the Phase 3 trials are listed below:

Blood and lymphatic disorders – Agranulocytosis, Hemolytic anemia, Lymphocytosis, Neutropenia, Eosinophilia
General disorders and administration site conditions – Infusion site inflammation, Injection site hematoma, Injection site thrombosis
Hepatobiliary disorders – Jaundice
Investigations – Increased blood lactate dehydrogenase, Prolonged prothrombin time
Nervous system disorders – Paresthesia, seizures, encephalopathy, coma, asterixis, neuromuscular excitability, myoclonia
Renal and urinary disorders – Tubulointerstitial nephritis
Reproductive and breast disorders – Vaginal inflammation
Hypersensitivity Reactions– Anaphylaxis, Angioedema, Erythema multiforme, Stevens-Johnson syndrome, Toxic epidermal necrolysis

Clinical Trials Experience in Pediatric Patients

Pediatric Patients Aged 3 months to less than 18 years

AVYCAZ was evaluated in 128 pediatric patients aged 3 months to < 18 years in two single-blind, randomized, active-controlled clinical trials, one in patients with cUTI and the other in patients with cIAI. Safety data from the two studies were pooled. The AVYCAZ dosing regimen was the same in both of these trials [see Dosage and Administration (2.2)] with a mean treatment duration of 6 days, and a maximum of 14 days. The regimen was selected to result in pediatric drug exposure comparable to that of adults, and in the cIAI trial, metronidazole was administered concurrently with AVYCAZ. Patients were randomized 3:1 to receive AVYCAZ or comparator, which was meropenem or cefepime in the cIAI and cUTI trials, respectively. The median age of patients treated with AVYCAZ was 8.6 years, and in the comparator group 7.4 years. The majority of patients treated with AVYCAZ were female (57%) and Caucasian (80%). An open-label single-dose pharmacokinetic (PK) and safety trial was conducted in pediatric patients with HABP/VABP and enrolled four patients aged 11.6 months to 9.4 years [see Clinical Pharmacology 12.3].

There were no deaths reported in the trials of cUTI, cIAI, and HABP/VABP in pediatric patients aged 3 months and older. Treatment discontinuation due to adverse reactions in the pediatric cUTI and cIAI trials occurred in 2.3% (3/128) of patients receiving AVYCAZ and 0/50 of patients receiving comparator drugs.

The most common adverse reactions occurring in greater than 3% of pediatric patients aged 3 months to < 18 years treated with AVYCAZ were vomiting, diarrhea, rash, and infusion site phlebitis.

Pediatric Patients less than 3 months of Age

AVYCAZ was also evaluated in a trial enrolling 46 pediatric patients less than three months of age as follows: infants > 28 days to < 3 months (N=17), term neonates from birth to 28 days, (N=13), pre-term neonates from birth (gestational age ≥ 31 weeks) to 28 days (N=16). The median age of patients treated with AVYCAZ was 24 days. In this single-arm trial, 25 patients with a suspected or confirmed bacterial infection received a single-dose of AVYCAZ and 21 patients with suspected or confirmed serious gram-negative infections received multiple doses of AVYCAZ [see Dosage and Administration (2.2)]. The demographics of patients treated with AVYCAZ were female (54%), male (46%); racial groups of White (78%), Asian (11%), Black or African American (9%); ethnicities of Not Hispanic or Latino (91.3%); Hispanic or Latino (4.3%). In patients treated with multiple doses of AVYCAZ [see Dosage and Administration (2.2)], the mean treatment duration was 6 days and maximum treatment duration was 12 days.

There was one death reported in the trial for pediatric patients less than 3 months of age. There were no treatment discontinuations due to adverse reactions. The most common adverse reactions occurring in greater than 3% of pediatric patients less than 3 months of age were vomiting and increased transaminases.

The safety profile of AVYCAZ in pediatric patients was similar to adults with cIAI, cUTI, and HABP/VABP treated with AVYCAZ.

6.2 Postmarketing Experience

The following adverse reactions and altered laboratory tests have been identified during post approval use of ceftazidime (a component of AVYCAZ), or other cephalosporin-class antibacterial drugs. Because these reactions are reported voluntarily from a population of uncertain size, it is not always possible to reliably estimate their frequency or establish a causal relationship to drug exposure.

Colitis, toxic nephropathy, hepatic dysfunction including cholestasis, hemorrhage, pancytopenia, aplastic anemia, prolonged prothrombin time, false-positive test for urinary glucose. Acute myocardial ischemia with or without myocardial infarction may occur as part of an allergic reaction.

7 DRUG INTERACTIONS

7.1 Probenecid

In vitro, avibactam is a substrate of OAT1 and OAT3 transporters which might contribute to the active uptake from the blood compartment, and thereby its excretion. As a potent OAT inhibitor, probenecid inhibits OAT uptake of avibactam by 56% to 70% in vitro and, therefore, has the potential to decrease the elimination of avibactam when co-administered. Because a clinical interaction study of AVYCAZ or avibactam alone with probenecid has not been conducted, co-administration of AVYCAZ with probenecid is not recommended [see Clinical Pharmacology (12.3)].

7.2 Drug/Laboratory Test Interactions

The administration of ceftazidime may result in a false-positive reaction for glucose in the urine with certain methods. It is recommended that glucose tests based on enzymatic glucose oxidase reactions be used.

8 USE IN SPECIFIC POPULATIONS

8.1 Pregnancy

Risk Summary

There are no adequate and well-controlled studies of AVYCAZ, ceftazidime, or avibactam in pregnant women. Neither ceftazidime nor avibactam were teratogenic in rats at doses 40 and 9 times the recommended human clinical dose. In the rabbit, at twice the exposure as seen at the human clinical dose, there were no effects on embryofetal development with avibactam.

The background risk of major birth defects and miscarriage for the indicated population is unknown. The background risk of major birth defects is 2-4% and of miscarriage is 15-20% of clinically recognized pregnancies within the general population. Because animal reproduction studies are not always predictive of human response, this drug should be used in pregnancy only if clearly needed.

Data

Animal Data

Ceftazidime

Reproduction studies have been performed in mice and rats at doses up to 40 times the human dose and showed no evidence of harm to the fetus due to ceftazidime.

Avibactam

Avibactam was not teratogenic in rats or rabbits. In the rat, intravenous studies with 0, 250, 500 and 1000 mg/kg/day avibactam during gestation days 6-17 showed no embryofetal toxicity at doses up to 1000 mg/kg/day, approximately 9 times the human dose based on exposure (AUC). In a rat pre- and post-natal study at up to 825 mg/kg/day intravenously (11 times the human exposure based on AUC), there were no effects on pup growth and viability. A dose-related increase in the incidence of renal pelvic and ureter dilatation was observed in female weaning pups that was not associated with pathological changes to renal parenchyma or renal function, with renal pelvic dilatation persisting after female weaning pups became adults.

Rabbits administered intravenous avibactam on gestation days 6-19 at 0, 100, 300 and 1000 mg/kg/day showed no effects on embryofetal development at a dose of 100 mg/kg, twice the human exposure (AUC). At higher doses, increased post-implantation loss, lower mean fetal weights, delayed ossification of several bones and other anomalies were observed.

8.2 Lactation

Risk Summary

Ceftazidime is excreted in human milk in low concentrations. It is not known whether avibactam is excreted into human milk, although avibactam was shown to be excreted in the milk of rats. No information is available on the effects of ceftazidime and avibactam on the breast-fed child or on milk production.

The developmental and health benefits of breastfeeding should be considered along with the mother’s clinical need for AVYCAZ and any potential adverse effects on the breastfed child from AVYCAZ or from the underlying maternal conditions.

Data

In a rat pre- and post-natal study at doses up to 825 mg/kg/day intravenously (11 times the human exposure based on AUC), the exposure to avibactam was minimal in the pups in comparison to the dams. Exposure to avibactam was observed in both pups and milk on PND 7.

8.4 Pediatric Use

The safety and effectiveness of AVYCAZ in the treatment of cUTI, cIAI, and HABP/VABP have been established in pediatric patients at least 31 weeks gestational age and older. Use of AVYCAZ is supported by evidence from adequate and well-controlled studies of AVYCAZ in adults with cUTI, cIAI, and HABP/VABP and additional pharmacokinetic and safety data from pediatric trials [see Clinical Pharmacology (12.3), Clinical Studies (14.1 and 14.2)].

The safety profile of AVYCAZ in pediatric patients was similar to adults with cIAI, cUTI, and HABP/VABP treated with AVYCAZ [see Adverse Reactions (6.1)].

The safety and effectiveness of AVYCAZ in the treatment of cUTI, cIAI, and HABP/VABP have not been established in pediatric patients less than 31 weeks gestational age.

8.5 Geriatric Use

Of the 1809 patients treated with AVYCAZ in the Phase 2 and Phase 3 clinical trials 621 (34.5%) were 65 years of age and older, including 302 (16.7 %) patients 75 years of age and older.

In the pooled Phase 2 and Phase 3 cIAI AVYCAZ clinical trials, 20% (126/630) of patients treated with AVYCAZ were 65 years of age and older, including 49 (7.8%) patients 75 years of age and older. The incidence of adverse reactions in both treatment groups was higher in older patients (≥ 65 years of age) and similar in both treatment groups; clinical cure rates for patients 65 years of age or older were 73.0% (73/100) in the AVYCAZ plus metronidazole arm and 78.6% (77/98) in the meropenem arm.

In the Phase 3 cUTI trial, 30.7% (157/511) of patients treated with AVYCAZ were 65 years of age or older, including 78 (15.3%) patients 75 years of age or older. The incidence of adverse reactions in both treatment groups was lower in older patients (≥ 65 years of age) and similar between treatment groups. Among patients 65 years of age or older in the Phase 3 cUTI trial, 66.1% (82/124) of patients treated with AVYCAZ had symptomatic resolution at Day 5 compared with 56.6% (77/136) of patients treated with doripenem. The combined response (microbiological cure and symptomatic response) observed at the test-of-cure (TOC) visit for patients 65 years of age or older were 58.1% (72/124) in the AVYCAZ arm and 58.8% (80/136) in the doripenem arm.

In the Phase 3 HABP/VABP trial, 54.1% (236/436) of patients treated with AVYCAZ were 65 years of age or older, including 129 (29.6%) patients 75 years of age or older. The incidence of adverse reactions in patients ≥ 65 years of age was similar to patients < 65 years of age. The 28-day all-cause mortality was similar between treatment groups for patients 65 years of age or older (12.7% [29/229] for patients in the AVYCAZ arm and 11.3% [26/230] for patients in the meropenem arm).

Ceftazidime and avibactam are known to be substantially excreted by the kidney; therefore, the risk of adverse reactions to ceftazidime and avibactam may be greater in patients with decreased renal function. Because elderly patients are more likely to have decreased renal function, care should be taken in dose selection and it may be useful to monitor renal function. Healthy elderly subjects had 17% greater exposure relative to healthy young subjects when administered the same single dose of avibactam, which may have been related to decreased renal function in the elderly subjects. Dosage adjustment for elderly patients should be based on renal function [see Dosage and Administration (2.2) and Clinical Pharmacology (12.3)].

8.6 Renal Impairment

Dosage adjustment is required in adult patients with moderately or severely impaired renal function (CrCl 50 mL/min or less). For patients with changing renal function, CrCl should be monitored at least daily, particularly early in treatment, and dosage of AVYCAZ adjusted accordingly. Both ceftazidime and avibactam are hemodialyzable; thus, AVYCAZ should be administered after hemodialysis on hemodialysis days [see Dosage and Administration (2.2) and Clinical Pharmacology (12.3)].

Dosage adjustment is also required in pediatric patients with renal impairment from 2 years to less than 18 years of age with eGFR 50 mL/min/1.73 m^2 or less. There is insufficient information to recommend a dosing regimen for pediatric patients younger than 2 years of age with renal impairment [see Dosage and Administration (2.3) and Clinical Pharmacology (12.3)].

10 OVERDOSAGE

In the event of overdose, discontinue AVYCAZ and institute general supportive treatment.

Ceftazidime and avibactam can be removed by hemodialysis. In subjects with end-stage renal disease (ESRD) administered 1 gram ceftazidime, the mean total recovery in dialysate following a 4-hour hemodialysis session was 55% of the administered dose. In subjects with ESRD administered 100 mg avibactam, the mean total recovery in dialysate following a 4-hour hemodialysis session started 1 hour after dosing was approximately 55% of the dose.

No clinical information is available on the use of hemodialysis to treat AVYCAZ overdosage [see Clinical Pharmacology (12.3)].

11 DESCRIPTION

AVYCAZ is an antibacterial combination product consisting of the semisynthetic cephalosporin ceftazidime pentahydrate and the beta-lactamase inhibitor avibactam sodium for intravenous administration.

Ceftazidime

Ceftazidime is a semisynthetic, beta-lactam antibacterial drug. It is the pentahydrate of (6R,7R,Z)-7-(2-(2-aminothiazol-4-yl)-2-(2-carboxypropan-2-yloxyimino)acetamido)-8-oxo-3-(pyridinium-1-ylmethyl)-5-thia-1-aza-bicyclo[4.2.0]oct-2-ene-2-carboxylate. Its molecular weight is 636.6. The empirical formula is C22H32N6O12S2.

Figure 1. Chemical structure of ceftazidime pentahydrate

Avibactam

Avibactam sodium chemical name is sodium [(2S,5R)-2-carbamoyl-7-oxo-1,6-diazabicyclo[3.2.1]octan-6-yl] sulfate. Its molecular weight is 287.23. The empirical formula is C7H10N3O6SNa.

Figure 2. Chemical structure of avibactam sodium

AVYCAZ 2.5 grams (ceftazidime and avibactam) for injection is a white to yellow sterile powder for constitution consisting of ceftazidime pentahydrate and avibactam sodium packaged in glass vials. The formulation also contains sodium carbonate.

Each AVYCAZ 2.5 grams single-dose vial contains ceftazidime 2 grams (equivalent to 2.601 grams sterile ceftazidime pentahydrate/sodium carbonate) and avibactam 0.5 grams (equivalent to 0.544 grams sterile avibactam sodium). The sodium carbonate content of the mixture is 236.5 mg/vial. The total sodium content of the mixture is approximately 146 mg (6.4 mEq)/vial.

12 CLINICAL PHARMACOLOGY

12.1 Mechanism of Action

AVYCAZ is an antibacterial drug [see Clinical Pharmacology (12.4)].

12.2 Pharmacodynamics

As with other beta-lactam antimicrobial drugs, the time that unbound plasma concentrations of ceftazidime exceed the AVYCAZ minimum inhibitory concentration (MIC) against the infecting organism has been shown to best correlate with efficacy in a neutropenic murine thigh infection model with Enterobacteriaceae and Pseudomonas aeruginosa. The time above a threshold concentration has been determined to be the parameter that best predicts the efficacy of avibactam in in vitro and in vivo nonclinical models.

Cardiac Electrophysiology

In a thorough QT study, a supratherapeutic dose of ceftazidime (3 grams) was investigated for QT effects in combination with a supratherapeutic dose of avibactam (2 grams) given as a 30-minute single infusion. No significant effect on QTcF interval was detected at peak plasma concentration or at any other time. The largest 90% upper bound for the placebo corrected mean change from baseline was 5.9 ms. There were no QTcF intervals greater than 450 ms, nor were there any QTcF interval changes from baseline greater than 30 ms.

12.3 Pharmacokinetics

The mean pharmacokinetic parameters for ceftazidime and avibactam in healthy adult male subjects with normal renal function after single and multiple 2-hour intravenous infusions of AVYCAZ 2.5 grams (ceftazidime 2 grams and avibactam 0.5 grams) administered every 8 hours are summarized in Table 14.

Pharmacokinetic parameters of ceftazidime and avibactam were similar for single and multiple dose administration of AVYCAZ and were similar to those determined when ceftazidime or avibactam were administered alone.

Table 14. Pharmacokinetic Parameters (Geometric Mean [%CV]) of Ceftazidime and Avibactam Following Administration of AVYCAZ 2.5 grams (ceftazidime 2 grams and avibactam 0.5 grams) in Healthy Adult Male Subjects
 | Ceftazidime |  | Avibactam
Parameter | Single AVYCAZ 2.5 gramsa Dose Administered as a 2-hour Infusion (n = 16) | Multiple AVYCAZ 2.5 gramsa Doses Administered every 8 hours as 2-hour Infusions for 11 Days (n = 16) | Single AVYCAZ 2.5 gramsa Dose Administered as a 2-hour Infusion (n = 16) | Multiple AVYCAZ 2.5 gramsa Doses Administered every 8 hours as 2-hour Infusions for 11 Days (n = 16)
Cmax (mg/L) | 88.1 (14) | 90.4 (16) | 15.2 (14) | 14.6 (17)
AUC (mg-h/L)b | 289 (15)c | 291 (15) | 42.1 (16)d | 38.2 (19)
T1/2 (h) | 3.27 (33)c | 2.76 (7) | 2.22 (31)d | 2.71 (25)
CL (L/h) | 6.93 (15)c | 6.86 (15) | 11.9 (16)d | 13.1 (19)
Vss (L) | 18.1 (20)c | 17 (16) | 23.2 (23)d | 22.2 (18)
CL = plasma clearance; Cmax = maximum observed concentration; T1/2 = terminal elimination half-life; Vss (L) = volume of distribution at steady state
a ceftazidime 2 grams and avibactam 0.5 grams
b AUC0-inf (area under concentration-time curve from time 0 to infinity) reported for single-dose administration; AUC0-tau (area under concentration curve over dosing interval) reported for multiple-dose administration
c n = 15
d n = 13

The Cmax and AUC of ceftazidime increase in proportion to dose. Avibactam demonstrated approximately linear pharmacokinetics across the dose range studied (50 mg to 2000 mg) for single intravenous administration. No appreciable accumulation of ceftazidime or avibactam was observed following multiple intravenous infusions of AVYCAZ 2.5 grams (ceftazidime 2 grams and avibactam 0.5 grams) administered every 8 hours for up to 11 days in healthy adults with normal renal function.

Distribution

Less than 10% of ceftazidime was protein bound. The degree of protein binding was independent of concentration. The binding of avibactam to human plasma proteins was low (5.7% to 8.2%) and was similar across the range of concentrations tested in vitro (0.5 to 50 mg/L).

The steady-state volumes of distribution of ceftazidime and avibactam were 17 L and 22.2 L, respectively, in healthy adults following multiple doses of AVYCAZ 2.5 grams (ceftazidime 2 grams and avibactam 0.5 grams) infused every 8 hours over 2 hours for 11 days.

Following administration of AVYCAZ 2.5 g (ceftazidime 2 grams and avibactam 0.5 grams) to healthy male subjects every 8 hours as a 2-hour infusion for 3 days, the mean bronchial epithelial lining fluid-to-plasma ratios of avibactam Cmax and AUC0-tau were 35%. The mean bronchial epithelial lining fluid-to-plasma ratios of ceftazidime Cmax and AUC0-tau were 26% and 31%, respectively.

Metabolism

Ceftazidime is mostly (80% to 90% of the dose) eliminated as unchanged drug. No metabolism of avibactam was observed in human liver preparations (microsomes and hepatocytes). Unchanged avibactam was the major drug-related component in human plasma and urine after a single intravenous dose of 0.5 grams ^14C-labelled avibactam.

Excretion

Both ceftazidime and avibactam are excreted mainly by the kidneys.

Approximately 80% to 90% of an intravenous dose of ceftazidime is excreted unchanged by the kidneys over a 24-hour period. After the intravenous administration of single 0.5-grams or 1-gram doses, approximately 50% of the dose appeared in the urine in the first 2 hours. An additional 20% was excreted between 2 and 4 hours after dosing, and approximately another 12% of the dose appeared in the urine between 4 and 8 hours later. The elimination of ceftazidime by the kidneys resulted in high therapeutic concentrations in the urine. The mean renal clearance of ceftazidime was approximately 100 mL/min. The calculated plasma clearance of approximately 115 mL/min indicated nearly complete elimination of ceftazidime by the renal route.

Following administration of a single 0.5-grams intravenous dose of radiolabeled avibactam, an average of 97% of administered radioactivity was recovered from the urine, with over 95% recovered within 12 hours of dosing. An average of 0.20% of administered total radioactivity was recovered in feces within 96 hours of dosing. An average of 85% of administered avibactam was recovered from the urine as unchanged drug within 96 hours, with over 50% recovered within 2 hours of the start of the infusion. Renal clearance was 158 mL/min, which is greater than the glomerular filtration, suggesting that active tubular secretion contributes to the excretion of avibactam in addition to glomerular filtration.

Specific Populations

Patients with Renal Impairment

Ceftazidime is eliminated almost solely by the kidneys; its serum half-life is significantly prolonged in patients with impaired renal function.

The clearance of avibactam was significantly decreased in subjects with mild (CrCl greater than 50 to 80 mL/min, n = 6), moderate (CrCl 30 to less than or equal to 50 mL/min, n = 6), and severe (CrCl 30 mL/min or less, not requiring hemodialysis; n = 6) renal impairment compared to healthy subjects with normal renal function (CrCl greater than 80 mL/min, n = 6) following administration of a single 100-mg intravenous dose of avibactam. The slower clearance resulted in increases in systemic exposure (AUC) of avibactam of 2.6-fold, 3.8-fold, and 7-fold in subjects with mild, moderate, and severe renal impairment, respectively, compared to subjects with normal renal function.

A single 100-mg dose of avibactam was administered to subjects with ESRD (n = 6) either 1 hour before or after hemodialysis. The avibactam AUC following the post-hemodialysis infusion was 19.5-fold the AUC of healthy subjects with normal renal function. Avibactam was extensively removed by hemodialysis, with an extraction coefficient of 0.77 and a mean hemodialysis clearance of 9.0 L/h. Approximately 55% of the avibactam dose was removed during a 4-hour hemodialysis session.

Dosage adjustment of AVYCAZ is recommended in adult and pediatric patients 2 years and older with moderate and severe renal impairment and end-stage renal disease. Population PK models for ceftazidime and avibactam were used to conduct simulations for patients with impaired renal function. Simulations demonstrated that the recommended dose adjustments [see Dosage and Administration (2.3)] provide comparable exposures of ceftazidime and avibactam in both adult and pediatric patients with moderate and severe renal impairment and end-stage renal disease to those in patients with normal renal function or mild renal impairment. Because the exposure of both ceftazidime and avibactam is highly dependent on renal function, monitor renal function (i.e., CrCl in adult patients and eGFR in pediatric patients) at least daily and adjust the dosage of AVYCAZ accordingly [see Dosage and Administration (2.3)]. There is insufficient information to recommend a dosage regimen for pediatric patients less than 2 years of age with renal impairment.

Patients with Hepatic Impairment

The presence of hepatic dysfunction had no effect on the pharmacokinetics of ceftazidime in individuals administered 2 grams intravenously every 8 hours for 5 days.

The pharmacokinetics of avibactam in patients with hepatic impairment have not been established. Avibactam does not appear to undergo significant hepatic metabolism; therefore, the systemic clearance of avibactam is not expected to be significantly affected by hepatic impairment.

Dose adjustments are not currently considered necessary for AVYCAZ in patients with impaired hepatic function.

Pediatric Patients

Population pharmacokinetic analyses and target attainment simulations were conducted to recommend AVYCAZ dosing in pediatric patients with cIAI, cUTI and HABP/VABP. The recommended pediatric dosing regimens for patients from 2 to less than 18 years of age with eGFR of greater than 50 mL/min/1.73 m^2 and for patients from birth (with gestational age 31 weeks and older) to less than 2 years without renal impairment are predicted to result in systemic exposures similar to that in adult patients given AVYCAZ 2.5 grams. Population PK modeling, including the assumption of proportional effects of renal impairment in adults and pediatric patients, also predicted that the recommended dose adjustments for patients aged 2 years and older with eGFR less than or equal to 50 mL/min/1.73 m^2 result in systemic exposure similar to that in adult patients. There is insufficient information to recommend a dosage adjustment in pediatric patients less than 2 years of age with renal impairment.

Geriatric Patients

Following single-dose administration of 0.5 grams avibactam as a 30-minute infusion the mean AUC for avibactam was 17% higher in healthy elderly subjects (65 years of age and older, n = 16) than in healthy young adult subjects (18 to 45 years of age, n = 17). There was no statistically significant age effect for avibactam Cmax.

No dose adjustment is recommended based on age. Dosage adjustment for AVYCAZ in elderly patients should be based on renal function [see Dosage and Administration (2.2)].

Gender

Following single-dose administration of 0.5 grams avibactam as a 30-minute infusion, healthy male subjects (n = 17) had 18% lower avibactam Cmax values than healthy female subjects (n = 16). There was no gender effect for avibactam AUC parameters.

No dose adjustment is recommended based on gender.

Drug Interactions

Avibactam at clinically relevant concentrations does not inhibit the cytochrome P450 isoforms CYP1A2, CYP2A6, CYP2B6, CYP2C8, CYP2C9, CYP2C19, CYP2D6, CYP2E1 and CYP3A4/5 in vitro in human liver microsomes. Avibactam showed no potential for in vitro induction of CYP1A2, 2B6, 2C9 and 3A4 isoenzymes in human hepatocytes. Against CYP2E1, avibactam showed a slight induction potential at very high concentrations that exceed any clinically relevant exposure. Ceftazidime was evaluated independently in human hepatocytes and showed no induction potential on the activity or mRNA expression of CYP1A1/2, CYP2B6, and CYP3A4/5.

Neither ceftazidime nor avibactam was found to be an inhibitor of the following hepatic and renal transporters in vitro at clinically relevant concentrations: MDR1, BCRP, OAT1, OAT3, OATP1B1, OATP1B3, BSEP, MRP4, OCT1 and OCT2. Avibactam was not a substrate of MDR1, BCRP, MRP4, or OCT2, but was a substrate of human OAT1 and OAT3 kidney transporters based on results generated in human embryonic kidney cells expressing these transporters. Probenecid inhibits 56% to 70% of the uptake of avibactam by OAT1 and OAT3 in vitro. Ceftazidime does not inhibit avibactam transport mediated by OAT1 and OAT3. The clinical impact of potent OAT inhibitors on the pharmacokinetics of avibactam is not known. Co-administration of AVYCAZ with probenecid is not recommended [see Drug Interactions (7.1)].

Administration of AVYCAZ 2.5 grams (ceftazidime 2 grams and avibactam 0.5 grams) to healthy male subjects (n = 28) as a 2-hour infusion following a 1-hour infusion of metronidazole every 8 hours for 3 days did not affect the Cmax and AUC values for avibactam or ceftazidime compared to administration of AVYCAZ 2.5 grams (ceftazidime 2 grams and avibactam 0.5 grams) alone. Administration of 0.5 grams metronidazole to healthy male subjects as a 1-hour infusion before a 2-hour infusion of AVYCAZ 2.5 grams (ceftazidime 2 grams and avibactam 0.5 grams) every 8 hours for 3 days did not affect the Cmax and AUC of metronidazole compared to administration of 0.5 grams metronidazole alone.

12.4 Microbiology

Mechanism of Action

The ceftazidime component of AVYCAZ is a cephalosporin antibacterial drug with in vitro activity against certain gram-negative and gram-positive bacteria. The bactericidal action of ceftazidime is mediated through binding to essential penicillin-binding proteins (PBPs). The avibactam component of AVYCAZ is a non-beta-lactam beta-lactamase inhibitor that inactivates certain beta-lactamases that degrade ceftazidime. Avibactam does not decrease the activity of ceftazidime against ceftazidime-susceptible organisms.

AVYCAZ demonstrated in vitro activity against Enterobacteriaceae in the presence of some beta-lactamases and extended-spectrum beta-lactamases (ESBLs) of the following groups: TEM, SHV, CTX-M, Klebsiella pneumoniae carbapenemase (KPCs), AmpC, and certain oxacillinases (OXA). AVYCAZ also demonstrated in vitro activity against P. aeruginosa in the presence of some AmpC beta-lactamases, and certain strains lacking outer membrane porin (OprD). AVYCAZ is not active against bacteria that produce metallo-beta lactamases and may not have activity against gram-negative bacteria that overexpress efflux pumps or have porin mutations.

Resistance

No cross-resistance with other classes of antimicrobials has been identified. Some isolates resistant to other cephalosporins (including ceftazidime) and to carbapenems may be susceptible to AVYCAZ.

Interaction with Other Antimicrobials

In vitro studies have not demonstrated antagonism between AVYCAZ and colistin, levofloxacin, linezolid, metronidazole, tigecycline, tobramycin, or vancomycin.

Activity against Ceftazidime-Nonsusceptible Bacteria in Animal Infection Models

Avibactam restored activity of ceftazidime in animal models of infection (e.g. thigh infection, pyelonephritis, systemic infection induced by intraperitoneal injection) caused by ceftazidime non-susceptible beta-lactamase- producing (e.g., ESBL, KPC and AmpC) gram-negative bacteria.

Antimicrobial Activity

AVYCAZ has been shown to be active against most isolates of the following bacteria, both in vitro and in clinical infections [see Indications and Usage (1.1), (1.2) and (1.3)].

Complicated Intra-abdominal Infections (cIAI)
Aerobic Bacteria

Gram-negative Bacteria

- Citrobacter freundii complex
- Enterobacter cloacae
- Escherichia coli
- Klebsiella oxytoca
- Klebsiella pneumoniae
- Proteus mirabilis
- Pseudomonas aeruginosa

Complicated Urinary Tract Infections (c UTI), including Pyelonephritis
Aerobic Bacteria

Gram-negative Bacteria

- Citrobacter freundii complex
- Enterobacter cloacae
- Escherichia coli
- Klebsiella pneumoniae
- Proteus mirabilis
- Pseudomonas aeruginosa

Hospital-acquired Bacterial Pneumonia and Ventilator-associated Bacterial Pneumonia (HABP/VABP)
Aerobic Bacteria

Gram-negative Bacteria

- Enterobacter cloacae
- Escherichia coli
- Haemophilus influenzae
- Klebsiella pneumoniae
- Proteus mirabilis
- Pseudomonas aeruginosa
- Serratia marcescens

The following in vitro data are available, but their clinical significance is unknown. At least 90 percent of the following bacteria exhibit an in vitro minimum inhibitory concentration (MIC) less than or equal to the susceptible breakpoint for AVYCAZ against isolates of similar genus or organism group. However, the efficacy of AVYCAZ in treating clinical infections caused by these bacteria has not been established in adequate and well-controlled clinical trials.

Gram-negative Bacteria

- Citrobacter koseri
- Enterobacter aerogenes
- Morganella morganii
- Providencia rettgeri
- Providencia stuartii

Susceptibility Test Methods

For specific information regarding susceptibility testing methods, interpretive criteria, and associated test methods and quality control standards recognized by FDA for AVYCAZ, please see: https://www.fda.gov/STIC.

13 NONCLINICAL TOXICOLOGY

13.1 Carcinogenesis, Mutagenesis, Impairment of Fertility

Ceftazidime and avibactam were each evaluated for mutagenic potential in several in vitro and in vivo assays. Ceftazidime was negative for mutagenicity in a mouse micronucleus test and an Ames test. Avibactam was negative for genotoxicity in the Ames assay, unscheduled DNA synthesis, chromosomal aberration assay, and a rat micronucleus study.

Avibactam had no adverse effects on fertility of male and female rats given up to 1 g/kg/day (approximately 20-fold higher than the recommended clinical dose on a body surface area basis). There was a dose-related increase in the percentage of pre- and post-implantation loss relative to controls, resulting in a lower mean litter size at doses 0.5 g/kg and greater with intravenous administration to female rats beginning 2 weeks prior to mating.

14 CLINICAL STUDIES

14.1 Complicated Intra-abdominal Infections

Adult Patients

A total of 1058 adults hospitalized with cIAI were randomized and received trial medications in a multinational, multi-center, double-blind trial comparing AVYCAZ 2.5 grams (ceftazidime 2 grams and avibactam 0.5 grams) intravenously every 8 hours plus metronidazole (0.5 grams intravenously every 8 hours) to meropenem (1 gram intravenously every 8 hours) for 5 to 14 days of therapy. Complicated intra-abdominal infections included appendicitis, cholecystitis, diverticulitis, gastric/duodenal perforation, perforation of the intestine, and other causes of intra-abdominal abscesses and peritonitis.

The microbiologically modified intent-to treat (mMITT) population, which included all patients who had at least one baseline intra-abdominal pathogen, consisted of 823 patients; the median age was 51 years and 62.8% were male. The majority of patients (64.9%) were from Eastern Europe; 7.5% were from the United States. Less than 1.0% of patients were of Pacific Island or African descent. The most common primary cIAI diagnosis was appendiceal perforation or peri-appendiceal abscess, occurring in 44.7% of patients. Bacteremia at baseline was present in 4.3% of patients.

Clinical cure was defined as complete resolution or significant improvement in signs and symptoms of the index infection at the test-of-cure (TOC) visit which occurred 28 to 35 days after randomization. Table 15 presents the clinical cure in the mMITT population and in the microbiologically evaluable (ME) population, which included all protocol-adherent mMITT patients. AVYCAZ plus metronidazole was non-inferior to meropenem with regard to the primary endpoint (clinical cure rate at the TOC visit in the mMITT population). Clinical cure rates at the TOC visit by pathogen in the mMITT population are presented in Table 16.

Table 15. Clinical Cure Rates at TOC from the Phase 3 cIAI Trial
Analysis population | AVYCAZ plus metronidazolea n/N (%) | Meropenemb n/N (%) | Treatment Difference (95% CI)c
mMITT | 337/413 (81.6) | 349/410 (85.1) | -3.5 (-8.6, 1.6)
ME | 244/265 (92.1) | 272/287 (94.8) | -2.7 (-7.1, 1.5)
a AVYCAZ 2.5 grams (ceftazidime 2 grams and avibactam 0.5 grams) IV every 8 hours + metronidazole 0.5 grams IV every 8 hours
b 1 gram IV every 8 hours
c The 95% confidence interval (CI) was calculated as an unstratified Miettinen and Nurminen method

Of the 823 patients in the mMITT population, 14 (1.7%) had baseline E. coli bacteremia; 7/10 (70.0%) of patients in the AVYCAZ arm and 3/4 (75.0%) of patients in the meropenem arm had a clinical cure.

Table 16. Clinical Cure Rates at TOC by Baseline Pathogen from the Phase 3 cIAI Trial, mMITT Population
Aerobic Gram-negative group or pathogen | AVYCAZ plus metronidazolea n/N (%) | Meropenemb n/N (%)
Enterobacteriaceae | 272/334 (81.4) | 305/353 (86.4)
Escherichia coli | 218/271 (80.4) | 248/285 (87.0)
Klebsiella pneumoniae | 40/51 (78.4) | 37/49 (75.5)
Klebsiella oxytoca | 14/18 (77.8) | 12/15 (80.0)
Enterobacter cloacae | 11/13 (84.6) | 16/19 (84.2)
Citrobacter freundii complex | 14/18 (77.8) | 9/12 (75.0)
Proteus mirabilis | 5/8 (62.5) | 7/9 (77.8)
Pseudomonas aeruginosa | 30/35 (85.7) | 34/36 (94.4)
a AVYCAZ 2.5 grams (ceftazidime 2 grams and avibactam 0.5 grams) IV every 8 hours + metronidazole 0.5 grams IV every 8 hours
b 1 gram IV every 8 hours

At baseline, 111 patients in the mMITT population had Gram-negative isolates that were not susceptible to ceftazidime, including 61 patients with E. coli and 26 patients with K. pneumoniae isolates. Cure rates were 39/47 (83.0%) in patients who received AVYCAZ and 55/64 (85.9%) of patients who received meropenem.

In a subset of Gram-negative pathogens from both arms of the Phase 3 cIAI trial that met phenotypic screening criteria for the presence of a beta-lactamase, genotypic testing identified certain ESBL groups (e.g., TEM-1, SHV-12, CTX-M-15, OXA-48) and AmpC that were expected to be inhibited by avibactam in isolates from 105 (12.8%) of the 823 patients in the mMITT population. Clinical cure rates in this subset were similar to the overall results.

Pediatric Patients

The pediatric cIAI trial was a randomized, single-blind, multi-center, active controlled trial conducted in hospitalized patients aged 3 months to less than 18 years. Patients were randomized in a 3:1 ratio to receive either AVYCAZ [see Dosage and Administration (2.2)] plus metronidazole (10 mg/kg IV over 20 to 30 minutes every 8 hours), or meropenem (20 mg/kg IV every 8 hours). Patients received IV treatment for a minimum of 72 hours before an optional switch to oral therapy at the discretion of the investigator to complete a total of 7 to 15 days of antibacterial therapy.

The intent-to treat (ITT) population consisted of 83 patients (AVYCAZ plus metronidazole, n=61, meropenem n=22) who were randomized to receive treatment; 64% were male, and the median age was 11.0 years in the AVYCAZ plus metronidazole group (range 3 to 17 years). The pediatric age groups who received AVYCAZ plus metronidazole were as follows: 12 to <18 years, (n=22), 6 to < 12 years, (n=33), 3 to < 6 years (n=6). No patients less than 2 years of age received AVYCAZ plus metronidazole. Most patients (87%) had a diagnosis of appendiceal perforation or peri-appendiceal abscess. The microbiological intent-to treat (micro-ITT) population, which included all patients who had at least one baseline intra-abdominal pathogen, consisted of 69 patients (AVYCAZ plus metronidazole, n=50; meropenem, n=19). The predominant baseline pathogens were E. coli (79.7%) and P. aeruginosa (33.3%).

The primary objective of the study was to evaluate the safety and tolerability of AVYCAZ and it was not powered for a statistical analysis of efficacy. At the TOC visit, which occurred 8 to 15 days after the last dose of study drug, a favorable clinical response was defined as the resolution of all acute signs and symptoms of cIAI or improvement to such an extent that no further antimicrobial therapy was required. The clinical cure rates for the trial at TOC are described in Table 17.

Table 17. Clinical Cure Rates at TOC from the Pediatric cIAI Trial
Analysis population | AVYCAZ plus metronidazolea n/N (%) | Meropenemb n/N (%)
ITT | 56/61 (91.8) | 21/22 (95.5)
Micro-ITT | 45/50 (90.0) | 18/19 (94.7)
a AVYCAZ doses as per Table 2, Dosage and Administration + metronidazole 10 mg/kg IV every 8 hours
b 20 mg/kg IV every 8 hours

Clinical cure rates for the predominant pathogens, E.coli and P.aeruginosa, were 90.5% and 85.7%, respectively for patients treated with AVYCAZ plus metronidazole, and 92.3% and 88.9%, respectively, for patients treated with meropenem.

14.2 Complicated Urinary Tract Infections, Including Pyelonephritis

Adult Patients

The efficacy of AVYCAZ in patients with cUTI was evaluated in two randomized, actively controlled clinical trials (Trial 1 and Trial 2) as described below.

cUTI Trial 1

A total of 1020 adults hospitalized with cUTI were randomized and received trial medications in a multinational, multi-center, double-blind trial comparing AVYCAZ 2.5 grams (ceftazidime 2 grams and avibactam 0.5 grams) intravenously every 8 hours to doripenem 0.5 grams intravenously every 8 hours for 10 to 14 days of total therapy. A switch to an oral antimicrobial agent was allowed after 5 days of intravenous dosing. Complicated urinary tract infections included acute pyelonephritis and complicated lower urinary tract infections.

The mMITT population, which included all patients who had at least one uropathogen isolated at baseline (greater or equal to 10^5 CFU/mL), consisted of 810 patients; the median age was 55 years and 69.8% were female. The majority of patients (75.4%) were from Eastern Europe; less than 1% of patients were from the United States. The majority of patients were White (83%) or Asian (7.8%); other racial subgroups were each represented at less than 1%. The most common diagnosis was acute pyelonephritis, occurring in 72% of patients. Bacteremia was present at baseline in 8.8% of patients.

Clinical efficacy was determined by comparing the response rate of AVYCAZ to doripenem at both primary endpoints; symptom response rates at Day 5 and combined microbiological cure and symptom response rates at the TOC visit (21 to 25 days after randomization). A symptom response was based on the resolution of patient-reported cUTI symptoms, defined as frequency/urgency/dysuria/suprapubic pain, as well as an improvement in flank pain for individuals with acute pyelonephritis. Microbiological cure was defined as a reduction of all baseline uropathogens to less than 10^4 CFU/mL in the urine.

AVYCAZ was non-inferior to doripenem with regard to both primary endpoints as presented in Table 18.

Table 18. Clinical and Microbiological Cure Rates from cUTI Trial 1, mMITT Population
Study endpoint | AVYCAZa n/N (%) | Doripenemb n/N (%) | Treatment Difference (95% CI)c
Symptomatic response at Day 5 | 276/393 (70.2) | 276/417 (66.2) | 4.0 (-2.4, 10.4)
Combined symptomatic and microbiological response at TOC | 280/393 (71.2) | 269/417 (64.5) | 6.7 (0.3, 13.1)
Microbiological cure at TOC | 304/393 (77.4) | 296/417 (71.0) | 6.4 (0.3, 12.4)
Symptomatic response at TOC | 332/393 (84.5) | 360/417 (86.3) | -1.9 (-6.8, 3.0)
a AVYCAZ 2.5 grams (ceftazidime 2 grams and avibactam 0.5 grams) IV every 8 hours
b 0.5 grams IV every 8 hours
c The 95% confidence interval (CI) was calculated using the unstratified Miettinen and Nurminen method

Microbiological cure rates by pathogen are presented in Table 19. Microbiological cure in individuals with bacteremia at baseline was achieved in 31/38 (81.6%) patients in the AVYCAZ arm and 24/33 (72.7%) patients in the doripenem arm at the TOC visit in the mMITT population. The most common pathogen isolated from blood was Escherichia coli, for which 31/32 (96.9%) patients in the AVYCAZ arm were microbiological cures, compared with 28/28 (100%) patients in the doripenem arm.

Table 19. Microbiological Cure Rate at TOC by Baseline Pathogen from cUTI Trial 1, mMITT Population
Aerobic Gram-negative group or pathogen | AVYCAZa n/N (%) | Doripenemb n/N (%)
Enterobacteriaceae | 299/382 (78.3) | 281/398 (70.6)
Escherichia coli | 229/292 (78.4) | 220/306 (71.9)
Klebsiella pneumoniae | 33/44 (75.0) | 35/56 (62.5)
Proteus mirabilis | 16/17 (94.1) | 9/13 (69.2)
Enterobacter cloacae | 6/11 (54.5) | 9/13 (69.2)
Pseudomonas aeruginosa | 12/18 (66.7) | 15/20 (75.0)
a AVYCAZ 2.5 grams (ceftazidime 2 grams and avibactam 0.5 grams) IV every 8 hours
b 0.5 grams IV every 8 hours

At baseline, 159 patients in the mMITT population had Gram-negative isolates that were not susceptible to ceftazidime, including 75 patients in the AVYCAZ arm and 84 in the doripenem arm. Microbiological and clinical cure rates at TOC were 47/75 (62.7%) and 67/75 (89.3%), respectively, in patients who received AVYCAZ, compared to 51/84 (60.7%) and 75/84 (89.3%) in patients who received doripenem.

In a subset of Gram-negative pathogens from both arms of the Phase 3 cUTI trial that met phenotypic screening criteria for the presence of a beta-lactamase, genotypic testing identified certain ESBL groups (e.g., TEM-1, SHV-12, CTX-M-15, CTX-M-27, OXA-48) and AmpC that were expected to be inhibited by avibactam in isolates from 176 (21.7%) of the 810 patients in the mMITT population. Microbiological and clinical cure rates in this subset were similar to the overall trial results.

cUTI Trial 2

In a multinational, multi-center, open-label study of adults hospitalized with ceftazidime non-susceptible (CAZ-NS) Gram-negative infections, 305 patients with cUTI were randomized and received AVYCAZ 2.5 grams (ceftazidime 2 grams and avibactam 0.5 grams) intravenously every 8 hours or the best available intravenous therapy (BAT) for 5 to 21 days of treatment. There was no optional switch to oral therapy. The majority (96.1%) of patients in the BAT arm received monotherapy with a carbapenem antibacterial drug. Complicated urinary tract infections included acute pyelonephritis and complicated lower urinary tract infections.

The mMITT population consisted of 281 cUTI patients with at least one baseline CAZ-NS uropathogen (defined as MIC greater or equal to 8 mg/L for Enterobacteriaceae and greater or equal to 16 mg/L for P. aeruginosa). The median age was 65 years and 54.8% were male. The majority of cUTI patients (82.2%) were from Eastern Europe; 2.8% were from the United States. The majority of patients (95%) were White. The most common diagnosis was cUTI without pyelonephritis, occurring in 54.8% of patients. Bacteremia at baseline was present in 3.6% of patients.

Clinical efficacy was based on evaluation of both the clinical cure (defined as resolution or significant improvement of baseline cUTI signs and symptoms) and microbiological cure (all baseline uropathogens were reduced to less than 10^4 CFU/mL) rates at the follow-up visit (21 to 25 calendar days from randomization) in the mMITT population.

The clinical and microbiological response rates at the follow-up visit in the mMITT population are presented in Table 20. The microbiological response rates at the follow-up visit by baseline CAZ-NS uropathogen in the mMITT population are presented in Table 21.

Table 20. Clinical and Microbiological Response Rates at Day 21 to 25 visit from Trial 2 (cUTI Patients), mMITT Population
Study Endpoint | AVYCAZa n/N (%) | BATb n/N (%) | Treatment Difference (95% CI) c
Combined clinical and microbiological cure | 101/144 (70.1) | 74/137 (54.0) | 16.1 (4.8, 27.1)
Clinical cure | 127/144 (88.2) | 121/137 (88.3) | -0.1 (-7.9, 7.7)
Microbiological cure | 103/144 (71.5) | 78/137 (56.9) | 14.6 (3.4, 25.5)
a AVYCAZ 2.5 grams (ceftazidime 2 grams and avibactam 0.5 grams) IV every 8 hours
b Best available therapy (BAT) options were meropenem, imipenem, doripenem, and colistin; the majority of patients received carbapenem monotherapy
c The 95% confidence interval (CI) was calculated using the unstratified Miettinen and Nurminen method

Table 21. Microbiological Response Rates by Baseline CAZ-NS Pathogen at the Day 21 to 25 visit from Trial 2 (cUTI Patients), mMITT Population
Aerobic Gram-negative pathogen | AVYCAZa n/N (%) | BATb n/N (%)
Enterobacteriaceae
Escherichia coli | 45/59 (76.3) | 33/57 (57.9)
Klebsiella pneumoniae | 42/55 (76.4) | 39/65 (60.0)
Pseudomonas aeruginosa | 8/14 (57.1) | 3/5 (60.0)
a AVYCAZ 2.5 grams (ceftazidime 2 grams and avibactam 0.5 grams) IV every 8 hours
b Best available therapy (BAT) options were meropenem, imipenem, doripenem, and colistin; the majority of patients received carbapenem monotherapy

Among Gram-negative uropathogens from both arms of Trial 2, genotypic testing identified certain ESBL groups (e.g., TEM-1, SHV-12, CTX-M-15, CTX-M-27, KPC-2, KPC-3, OXA-48) and AmpC beta-lactamases expected to be inhibited by avibactam in isolates from 273/281 (97.2%) patients in the mMITT population. Clinical and microbiological cure rates in this subset were similar to the overall results.

Pediatric Patients

The cUTI pediatric trial was a randomized, single-blind, multi-center, active-controlled study conducted in hospitalized patients aged 3 months to less than 18 years. Patients were randomized in a 3:1 ratio to receive either AVYCAZ [see Dosage and Administration (2.2)] or cefepime (dosed per local standard of care, and not to exceed 2000 mg per infusion). Patients received IV treatment for a minimum of 72 hours before an optional switch to oral therapy at the discretion of the investigator to complete a total of 7 to 14 days of antibacterial therapy.

A study population of 95 patients with cUTI received study medication (AVYCAZ, n=67, cefepime n=28); 81% were female, and the median age was 4.2 years in the AVYCAZ group (range 3.5 months to 18 years). The pediatric age groups who received AVYCAZ were as follows: 12 to <18 years, (n=13), 6 to < 12 years, (n=17), 2 to < 6 years (n=11), 1 to < 2 years (n=12), and 3 months to < 1 year of age (n=14). Most patients had a diagnosis of acute pyelonephritis (83%). The micro-ITT population consisted of 77 patients with at least one Gram-negative uropathogen at baseline (greater or equal to 10^5 CFU/mL). The predominant baseline pathogen was E. coli (92.2%).

The primary objective of the study was to evaluate the safety and tolerability of AVYCAZ and it was not powered for a statistical analysis of efficacy. At the TOC visit, which occurred 8 to 15 days after the last dose of study drug, a favorable clinical response was defined as a resolution of all acute signs and symptoms of cUTI or improvement to such an extent that no further antimicrobial therapy was required. A favorable microbiological response at the TOC was defined as eradication of baseline uropathogen(s) from the urine culture.

A summary of clinical, microbiological and combined response at TOC by treatment group for the micro-ITT population is provided in Table 22.

Table 22. Clinical and Microbiological Response Rates from the Pediatric cUTI Trial, micro-ITT Population
Study Endpoint | AVYCAZa n/N (%) | Cefepimeb n/N (%)
Combined clinical and microbiological cure | 39/54 (72.2) | 14/23 (60.9)
Clinical cure | 48/54 (88.9) | 19/23 (82.6)
Microbiological cure | 43/54 (79.6) | 14/23 (60.9)
a AVYCAZ doses as per Table 2, [see Dosage and Administration (2.2)]
b Dosed per local standard of care, and did not exceed 2000 mg

The microbiologic response rate for E.coli, the most common uropathogen identified in the study, was 79.6% for patients treated with AVYCAZ and 59.1% for patients treated with cefepime.

14.3 Hospital-acquired Bacterial Pneumonia and Ventilator-associated Bacterial Pneumonia

A total of 870 hospitalized adults with HABP/VABP were randomized and received trial medications in a multinational, multi-center, double-blind trial comparing AVYCAZ 2.5 grams (ceftazidime 2 grams and avibactam 0.5 grams) intravenously every 8 hours to meropenem 1 gram intravenously every 8 hours for 7 to 14 days of therapy. Study medication dosages were adjusted per renal function. The protocol allowed for administration of prior and concomitant systemic antibacterial therapy.

Clinical efficacy was evaluated in the intent-to treat (ITT) population, which included all randomized patients who received study drug. The median age was 66 years and 74.1% were male. The median APACHE II score was 14. The majority of patients were from China (33.1%) and Eastern Europe (25.5%). There were no patients enrolled within the United States. Less than 1.0% of patients were of Pacific Island or African descent. Overall, 379 (43.6%) patients were ventilated at enrollment, including 290 (33.3%) patients with VABP and 89 (10.2%) with ventilated HABP. Bacteremia at baseline was present in 4.8% of patients.

In the AVYCAZ and meropenem treatment groups up to 26% of patients received more than 24 hours of potentially effective systemic Gram-negative antibacterial therapy in the 3 days prior to randomization. Patients with infections only due to Gram-positive organisms were excluded from the trial, when this could be determined before enrollment. Following randomization, patients in both treatment groups could receive empiric open-label linezolid or vancomycin to cover for Gram-positive pathogens while awaiting culture results. Treatment with Gram-positive coverage continued in patients with Gram-positive pathogens.

Adjunctive Gram-negative antibacterial therapy with amikacin or another aminoglycoside was permitted if resistance to meropenem was suspected. Systemic Gram-negative antibacterial therapy was administered to 87% and 86% of patients in the AVYCAZ and meropenem treatment groups, respectively, at any point up to the end of therapy. In either treatment group, up to 36% of patients received more than 72 hours of potentially effective concomitant therapy.

Table 23 presents the 28-day all-cause mortality rates (28 to 32 days after randomization). Results are presented for the ITT population and for the microbiological intent-to-treat (micro-ITT) population, which included all patients with positive culture results indicating the presence of at least one Gram-negative pathogen. Clinical cure at the TOC visit (21-25 days from randomization) is also presented. Clinical cure was defined as resolution or significant improvement in signs and symptoms associated with pneumonia and cessation of antibacterial treatment for HABP/VABP. AVYCAZ was non-inferior to meropenem with regard to the primary endpoint (28-day all-cause mortality in the ITT population). The control group mortality rates were lower than that observed in other HABP/VABP trials which may impact generalizability of results. However, review of patient characteristics reflecting disease severity indicates the study enrolled a representative HABP/VABP population.

Table 23. 28-Day All-cause Mortality and Clinical Cure Rates from the Phase 3 HABP/VABP Trial, ITT and micro-ITT Populations
Study Endpoint (Population) | AVYCAZa n/N (%) | Meropenemb n/N (%) | Treatment Difference (95% CI) c
28-Day all-cause mortality (ITT) | 42/436 (9.6) | 36/434 (8.3) | 1.5 (- 2.4, 5.3) c
micro-ITT | 22/187 (11.8) | 19/195 (9.7) | 2.1 (- 4.1, 8.4) c
Clinical cure (ITT) | 293/436 (67.2) | 300/434 (69.1) | - 1.9 (- 8.1, 4.3) d, e
a AVYCAZ 2.5 grams (ceftazidime 2 grams and avibactam 0.5 grams) IV every 8 hours
b 1 gram IV every 8 hours
c The 95% confidence interval (CI) was calculated based on Greenwood’s variance estimates.
d A quantitative estimate of treatment effect has not been established for the clinical cure endpoint.
e The 95% confidence interval (CI) was calculated using an unstratified Miettinen and Nurminen method.

The administration of prior or concomitant Gram-negative antibacterial therapy can confound the assessment of trial results. However, a subgroup analysis of 28-day all-cause mortality in subjects who received 24 hours or less of potentially effective antibacterial therapy prior to randomization and 72 hours or less of concomitant potentially effective antibacterial therapy following randomization produced results similar to the overall ITT population, AVYCAZ mortality 10.0% (20/200), meropenem 6.2% (12/195) [difference 3.8%; 95% CI: -1.6 % to 9.5%]). In the subset of patients who received more than 24 hours of potentially effective antibacterial therapy prior to randomization or more than 72 hours of concomitant potentially effective antibacterial therapy following randomization, results were similar to the overall ITT population (AVYCAZ 9.7% (25/258), meropenem 10.5% (28/266) [difference -0.08%; 95% CI: (-6.1% to 4.4%)]).

All-cause mortality rates by pathogen are presented in Table 24. Of the 382 patients in the micro-ITT population, 36 patients were bacteremic at baseline; 20/21 (95.2%) in the AVYCAZ arm and 13/15 (86.7%) in the meropenem arm survived through the day-28 follow-up visit; 13/21 (61.9%) patients in the AVYCAZ arm and 9/15 (60%) of patients in the meropenem arm had a clinical cure at the TOC visit.

The 28-day all-cause mortality rates by pathogen in the micro-ITT population are presented in Table 24. The clinical cure rates at TOC by pathogen in the micro-ITT population are presented in Table 25.

Table 24. 28-Day All-cause Mortality by Baseline Pathogen from the Phase 3 HABP/VABP Trial, micro-ITT Population
Aerobic Gram-negative group or pathogen | AVYCAZa n/N (%) | Meropenemb n/N (%)
Enterobacteriaceae
Klebsiella pneumoniae | 11/65 (16.9) | 9/75 (12.0)
Enterobacter cloacae | 0/29 (0) | 4/23 (17.4)
Escherichia coli | 4/22 (18.2) | 3/23 (13.0)
Serratia marcescens | 0/15 (0) | 0/13 (0)
Proteus mirabilis | 1/14 (7.1) | 1/12 (8.3)
Haemophilus influenzae | 1/16 (6.3) | 2/25 (8.0)
Pseudomonas aeruginosa | 9/64 (14.1) | 4/51 (7.8)
a AVYCAZ 2.5 grams (ceftazidime 2 grams and avibactam 0.5 grams) IV every 8 hours
b 1 gram IV every 8 hours

Table 25. Clinical Cure Rates at TOC by Baseline Pathogen from the Phase 3 HABP/VABP Trial, micro-ITT Population
Aerobic Gram-negative group or pathogen | AVYCAZa n/N (%) | Meropenemb n/N (%)
Enterobacteriaceae | 92/133 (69.2) | 108/147 (73.5)
Klebsiella pneumoniae | 44/65 (67.7) | 56/75 (74.7)
Enterobacter cloacae | 25/29 (86.2) | 13/23 (56.5)
Escherichia coli | 12/22 (54.5) | 17/23 (73.9)
Serratia marcescens | 11/15 (73.3) | 12/13 (92.3)
Proteus mirabilis | 12/14 (85.7) | 9/12 (75.0)
Haemophilus influenzae | 13/16 (81.3) | 20/25 (80.0)
Pseudomonas aeruginosa | 38/64 (59.4) | 37/51 (72.5)
a AVYCAZ 2.5 grams (ceftazidime 2 grams and avibactam 0.5 grams) IV every 8 hours
b 1 gram IV every 8 hours

At baseline, 108/382 (28.3%) of patients in the micro-ITT population had Gram-negative isolates that were not susceptible to ceftazidime, including 53 patients with K. pneumoniae and 28 patients with P. aeruginosa isolates. The 28-day all-cause mortality in patients with ceftazidime non-susceptible Gram-negative isolates was 8.2% (4/49) in the AVYCAZ arm and 8.5% (5/59) in the meropenem arm. Clinical cure rates at TOC were 37/49 (75.5%) in patients who received AVYCAZ and 42/59 (71.2%) in patients who received meropenem.

16 HOW SUPPLIED/STORAGE AND HANDLING

AVYCAZ 2.5 grams (ceftazidime and avibactam) for injection is supplied as a white to yellow sterile powder for constitution in single-dose, clear glass vial containing: ceftazidime 2 grams and avibactam 0.5 grams. Vials are supplied as individual vial (NDC# 0456-2700-01) and in cartons containing 10 vials (NDC# 0456-2700-10).

AVYCAZ vials should be stored at 25°C (77°F); excursions permitted between 15°C and 30°C (59°F and 86°F) [See USP Controlled Room Temperature]. Protect from light. Store in carton until time of use.

Storage conditions for constituted and diluted solutions of AVYCAZ for injection are described in another section of labeling [see Dosage and Administration (2.4, 2.6)].

17 PATIENT COUNSELING INFORMATION

Serious Allergic Reactions

Advise patients, their families, or caregivers that allergic reactions, including serious allergic reactions, could occur that require immediate treatment. Ask them about any previous hypersensitivity reactions to AVYCAZ, other beta-lactams (including cephalosporins), or other allergens [see Warnings and Precautions (5.2)].

Potentially Serious Diarrhea

Advise patients, their families, or caregivers that diarrhea is a common problem caused by antibacterial drugs. Sometimes, frequent watery or bloody diarrhea may occur and may be a sign of a more serious intestinal infection. If severe watery or bloody diarrhea develops, tell them to contact his or her healthcare provider [see Warnings and Precautions (5.3)].

Nervous System Reactions

Advise patients, their families, or caregivers that neurological adverse reactions can occur with AVYCAZ use. Instruct patients their families, or caregivers to inform a healthcare provider at once of any neurological signs and symptoms, including encephalopathy (disturbance of consciousness including confusion, hallucinations, stupor, and coma), myoclonus, and seizures, for immediate treatment, dosage adjustment, or discontinuation of AVYCAZ [see Warnings and Precautions (5.4)].

Antibacterial Resistance

Patients should be counseled that antibacterial drugs including AVYCAZ should only be used to treat bacterial infections. They do not treat viral infections (e.g., the common cold). When AVYCAZ is prescribed to treat a bacterial infection, patients should be told that although it is common to feel better early in the course of therapy, the medication should be taken exactly as directed. Skipping doses or not completing the full course of therapy may (1) decrease the effectiveness of the immediate treatment and (2) increase the likelihood that bacteria will develop resistance and will not be treatable by AVYCAZ or other antibacterial drugs in the future [see Warnings and Precautions (5.5)].

Distributed by:
AbbVie, Inc.
North Chicago, IL 60064, USA

Manufactured by:
ACS Dobfar SpA
Via Alessandro Fleming, 2
Verona 37135, Italy

AVYCAZ® and its designs are trademarks of Allergan Sales, LLC, an AbbVie company.
© 2025 AbbVie. All rights reserved.

V4.0USPI2700

PACKAGE LABEL

PRINCIPAL DISPLAY PANEL
NDC 0456-2700-10
Rx only
Avycaz®